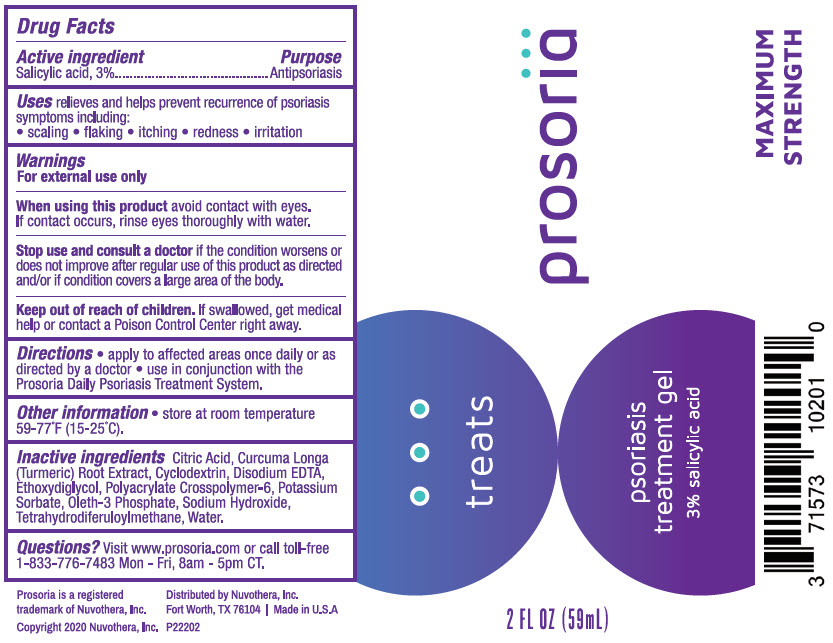 DRUG LABEL: Prosoria Psoriasis Treatment
NDC: 71573-102 | Form: GEL
Manufacturer: Nuvothera, Inc.
Category: otc | Type: HUMAN OTC DRUG LABEL
Date: 20240110

ACTIVE INGREDIENTS: Salicylic Acid 1.77 g/59 mL
INACTIVE INGREDIENTS: Water; Diethylene Glycol Monoethyl Ether; Tetrahydrodiferuloylmethane; TURMERIC; GAMMA CYCLODEXTRIN; Oleth-3 Phosphate; Edetate Disodium Anhydrous; Sodium Hydroxide; Potassium Hydroxide; Potassium Sorbate; Citric Acid Monohydrate

Prosoria Psoriasis Treatment

Drug Facts

Active ingredient

Salicylic acid, 3%

Purpose

Antipsoriasis

Uses

relieves and helps prevent recurrence of psoriasis symptoms including:

- scaling
- flaking
- itching
- redness
- irritation

Warnings

For external use only

When using this product avoid contact with eyes. If contact occurs, rinse eyes thoroughly with water.

Stop use and consult a doctor if the condition worsens or does not improve after regular use of this product as directed and/or if condition covers a large area of the body.

Keep out of reach of children. If swallowed, get medical help or contact a Poison Control Center right away.

Directions

- apply to affected areas once daily or as directed by a doctor
- use in conjunction with the Prosoria Daily Psoriasis Treatment System.

Other information

- store at room temperature 59-77°F (15-25°C).

Inactive ingredients

Citric Acid, Curcuma Longa (Turmeric) Root Extract, Cyclodextrin, Disodium EDTA, Ethoxydiglycol, Polyacrylate Crosspolymer-6, Potassium Sorbate, Oleth-3 Phosphate, Sodium Hydroxide, Tetrahydrodiferuloylmethane, Water.

Questions?

Visit www.prosoria.com or call toll-free 1-833-776-7483 Mon - Fri, 8am - 5pm CT.

Distributed by Nuvothera, Inc.
Fort Worth, TX 76104

PRINCIPAL DISPLAY PANEL - 59 mL Bottle Label

prosoria

MAXIMUM
STRENGTH

treats

psoriasis
treatment gel
3% salicylic acid

2 FL OZ (59mL)